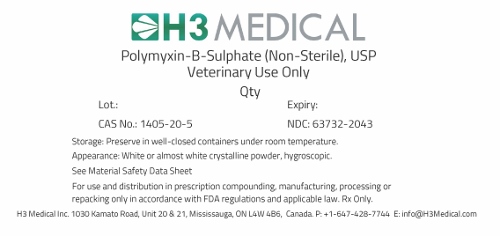 DRUG LABEL: Polymyxin B Sulphate
NDC: 63732-2043 | Form: POWDER
Manufacturer: H3 Medical Inc
Category: other | Type: BULK INGREDIENT
Date: 20180605

ACTIVE INGREDIENTS: POLYMYXIN B SULFATE 1 g/1 g

Polymyxin B Sulphate